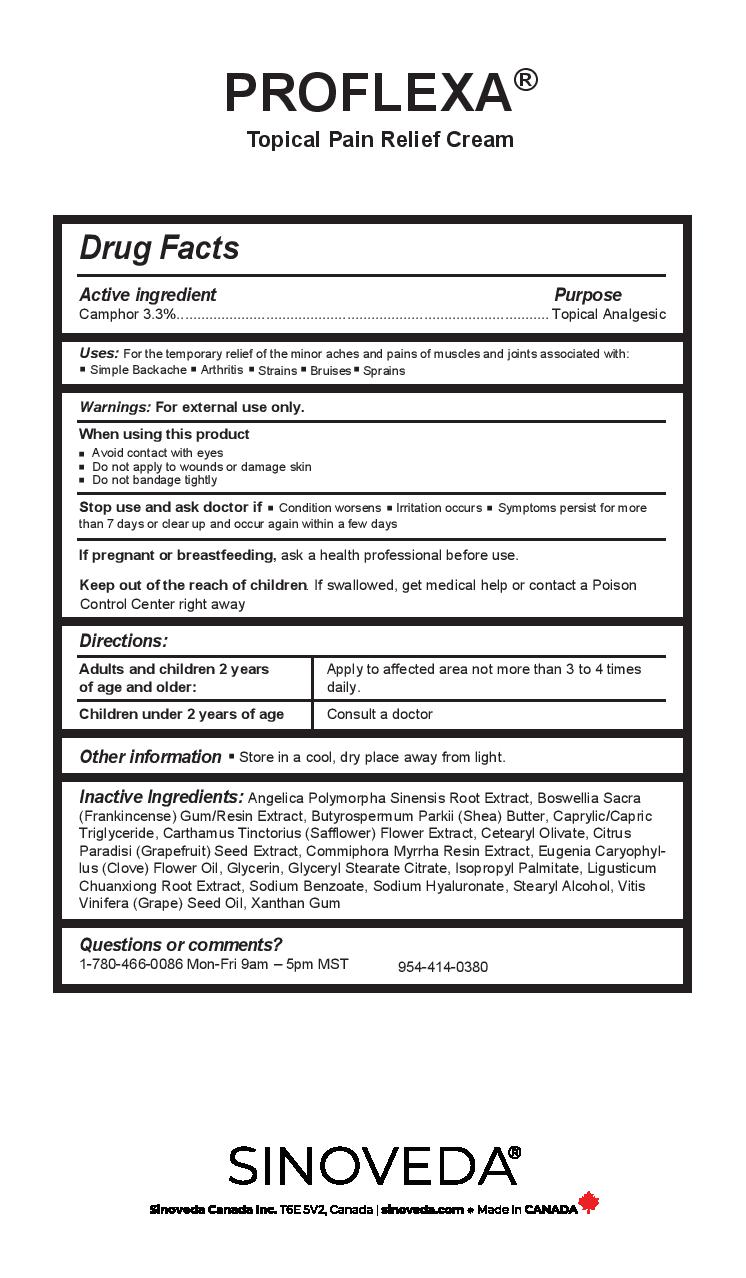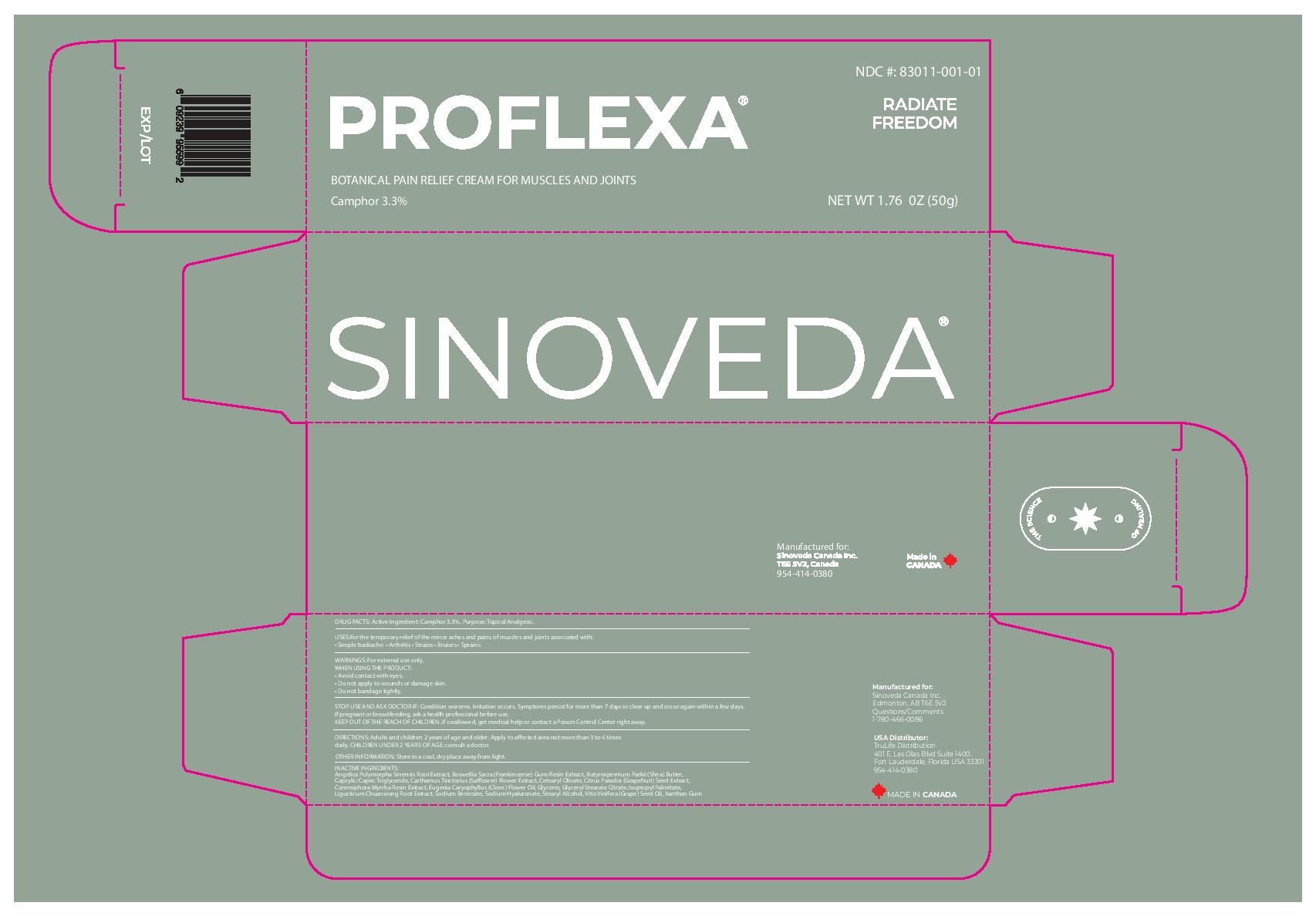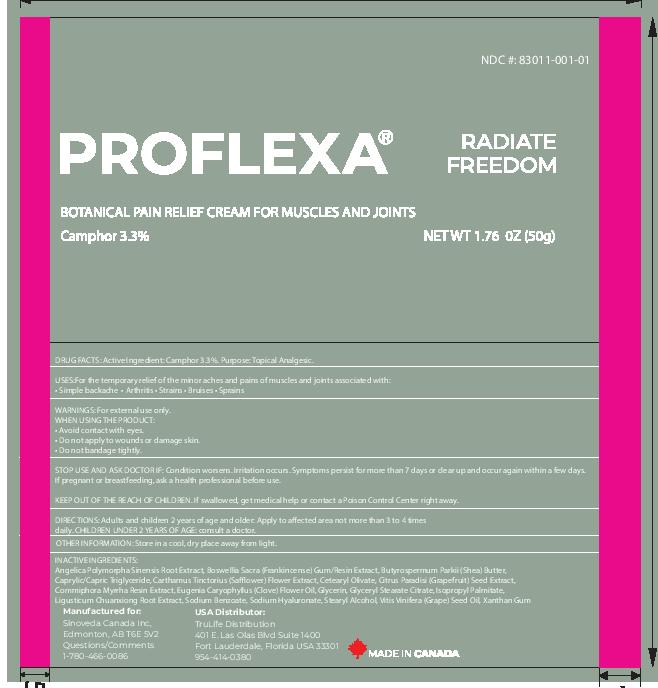 DRUG LABEL: Proflexa
NDC: 83011-001 | Form: CREAM
Manufacturer: Sinoveda Canada Inc
Category: otc | Type: HUMAN OTC DRUG LABEL
Date: 20220930

ACTIVE INGREDIENTS: CAMPHOR (NATURAL) 3.3 g/100 g
INACTIVE INGREDIENTS: SAFFLOWER; CETEARYL OLIVATE; CITRUS PARADISI SEED; MYRRH; GLYCERIN; GLYCERYL STEARATE CITRATE; ISOPROPYL PALMITATE; LIGUSTICUM SINENSE SUBSP. CHUANXIONG ROOT; SODIUM BENZOATE; HYALURONATE SODIUM; STEARYL ALCOHOL; GRAPE SEED OIL; XANTHAN GUM; ANGELICA POLYMORPHA ROOT; BOSWELLIA SACRA WHOLE; SHEA BUTTER; MEDIUM-CHAIN TRIGLYCERIDES; CLOVE OIL

Proflexa

Active ingredient

Camphor 3.3%

Purpose

Camphor 3.3%......................Topical Analgesic

Uses

For the temporary relief of the minor aches and pains of muscles and joints associated with:

- Simple Backache
- Arthritis
- Strains
- Bruises
- Sprains

Warnings

For external use only

When using this product

- Avoid contact with eyes
- Do not apply to wounds or damaged skin
- Do not bandage tightly

Stop use and ask doctor if

- Condition worsens
- Irritation occurs
- Symptoms persist for more than 7 days or clear up and occur again within a few days

PREGNANCY OR BREAST FEEDING

If pregnant or breastfeeding, ask a health professional before use.

Keep out of reach of children. If swallowed, get medical help or contact a Poison Control Center right away.

Directions

Adults and children 2 years of age and older: Apply to affected area not more than 3 to 4 times daily

Children under 2 years of age: Consult a doctor

Other information

Store in a cool, dry place away from light

Inactive ingredients

Angelica Polymorpha Sinensis Root Extract, Boswellia Sacra (Frankincense) Gum/Resin Extract, Butyrospermum Parkii (Shea) Butter, Caprylic/Capric Triglyceride, Carthamus Tinctorius (Safflower) Flower Extract, Cetearyl Olivate, Citrus Paradisi (Grapefruit) Seed Extract, Commiphora Myrrha Resin Extract, Eugenia Caryophyllus (Clove) Flower Oil, Glycerin, Glyceryl Stearate Citrate, Isopropyl Palmitate, Ligusticum Chuanxiong Root Extract, Sodium Benzoate, Sodium Hyaluronate, Stearyl Alcohol, Vitis Vinifera (Grape) Seed Oil, Xanthan Gum

Questions or comments?

1-780-466-0086 Mon-Fri 9am-5pm MST

954-414-0380

PACKAGE LABEL

Proflexa

Botanical Pain Relief Cream for Muscles and Joints

Camphor 3.3%

NDC #: 83011-001-01

Radiate Freedom

Net Wt 1.76 oz (50g)